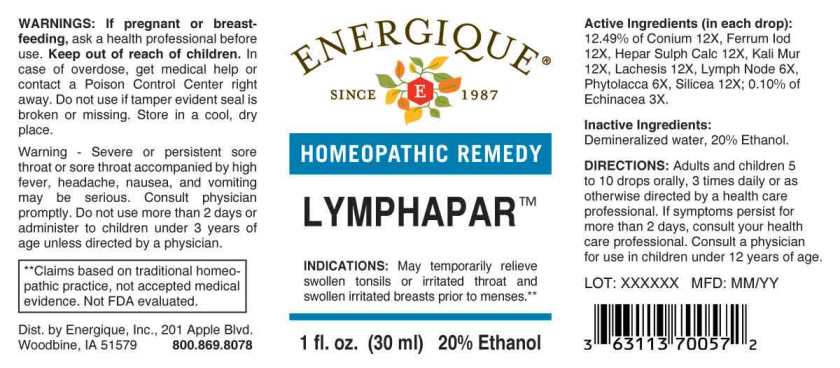 DRUG LABEL: Lymphapar
NDC: 44911-0456 | Form: LIQUID
Manufacturer: Energique, Inc.
Category: homeopathic | Type: HUMAN OTC DRUG LABEL
Date: 20240923

ACTIVE INGREDIENTS: ECHINACEA ANGUSTIFOLIA 3 [hp_X]/1 mL; SUS SCROFA LYMPH 6 [hp_X]/1 mL; PHYTOLACCA AMERICANA ROOT 6 [hp_X]/1 mL; CONIUM MACULATUM FLOWERING TOP 12 [hp_X]/1 mL; FERROUS IODIDE 12 [hp_X]/1 mL; CALCIUM SULFIDE 12 [hp_X]/1 mL; POTASSIUM CHLORIDE 12 [hp_X]/1 mL; LACHESIS MUTA VENOM 12 [hp_X]/1 mL; SILICON DIOXIDE 12 [hp_X]/1 mL
INACTIVE INGREDIENTS: WATER; ALCOHOL

Drug Facts:

ACTIVE INGREDIENTS:

(in each drop): 12.49% of Conium Maculatum 12X, Ferrum Iodatum 12X, Hepar Sulphuris Calcareum 12X, Kali Muriaticum 12X, Lachesis Mutus 12X, Lymph Node (Suis) 6X, Phytolacca Decandra 6X, Silicea 12X; 0.10% of Echinacea (Angustifolia) 3X.

INDICATIONS:

May temporarily relieve swollen tonsils or irritated throat and swollen irritated breasts prior to menses.**

**Claims based on traditional homeopathic practice, not accepted medical evidence. Not FDA evaluated.

WARNINGS:

If pregnant or breast-feeding, ask a health professional before use.

Keep out of reach of children. In case of overdose, get medical help or contact a Poison Control Center right away.

Do not use if tamper evident seal is broken or missing. Store in a cool, dry place.

Keep out of reach of children. In case of overdose, get medical help or contact a Poison Control Center right away.

DIRECTIONS:

Adults and children 5 to 10 drops orally, 3 times daily or as otherwise directed by a health care professional. If symptoms persist for more than 2 days, consult your health care professional. Consult a physician for use in children under 12 years of age.

INDICATIONS:

May temporarily relieve swollen tonsils or irritated throat and swollen irritated breasts prior to menses.**

**Claims based on traditional homeopathic practice, not accepted medical evidence. Not FDA evaluated.

INACTIVE INGREDIENTS:

Demineralized water, 20% Ethanol.

QUESTIONS:

Dist. by Energique, Inc.

201 Apple Blvd

Woodbine, IA 51579 800.869.8078

PACKAGE LABEL DISPLAY:

ENERGIQUE

SINCE 1987

HOMEOPATHIC REMEDY

LYMPHAPAR

1 fl. oz. (30 ml)